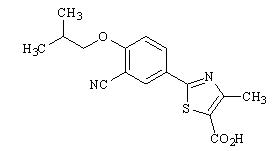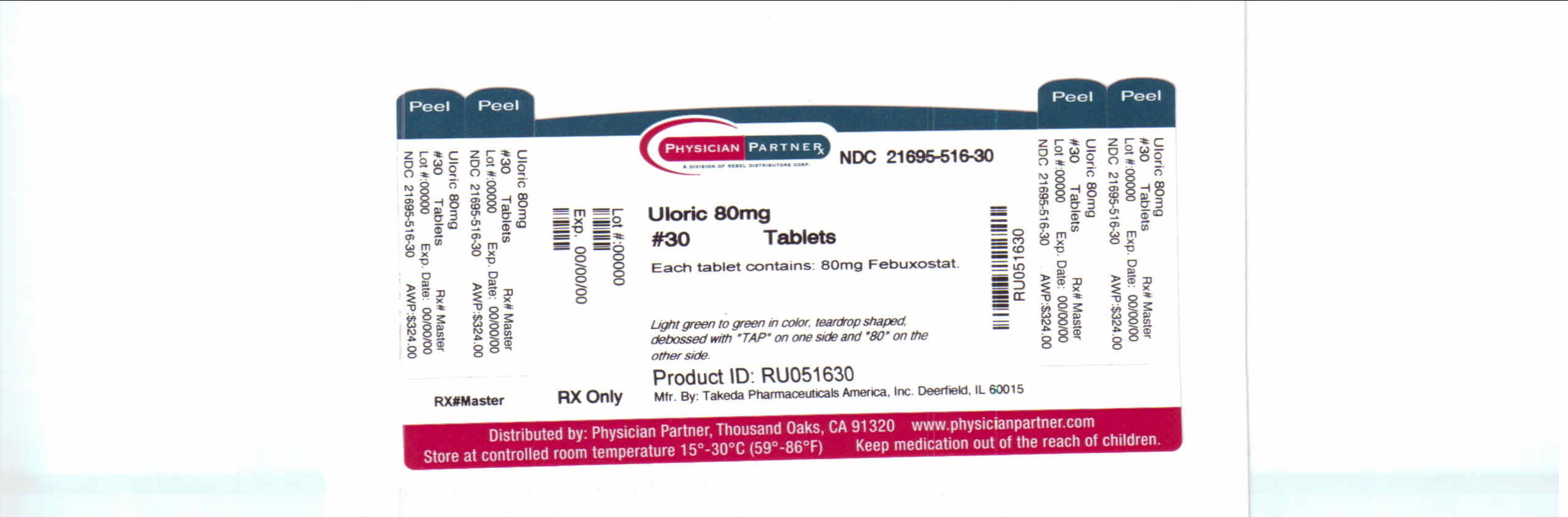 DRUG LABEL: ULORIC
NDC: 21695-516 | Form: TABLET
Manufacturer: Rebel Distributors Corp
Category: prescription | Type: HUMAN PRESCRIPTION DRUG LABEL
Date: 20101227

ACTIVE INGREDIENTS: febuxostat 80 mg/1 1
INACTIVE INGREDIENTS: lactose monohydrate; cellulose, microcrystalline; hydroxypropyl cellulose; croscarmellose sodium; silicon dioxide; magnesium stearate

HIGHLIGHTS OF PRESCRIBING INFORMATION

These HIGHLIGHTS do not include all the information needed to use ULORIC safely and effectively. See full prescribing information for ULORIC.
ULORIC (febuxostat) tablet for oral use
Initial U.S. Approval: 2009

1 INDICATIONS AND USAGE

ULORIC is a xanthine oxidase (XO) inhibitor indicated for the chronic management of hyperuricemia in patients with gout. (1)

ULORIC is not recommended for the treatment of asymptomatic hyperuricemia. (1)

2 DOSAGE AND ADMINISTRATION

- ULORIC is recommended at 40 mg or 80 mg once daily. The recommended starting dose of ULORIC is 40 mg once daily. For patients who do not achieve a serum uric acid (sUA) less than 6 mg per dL after 2 weeks with 40 mg, ULORIC 80 mg is recommended. (2.1)
- ULORIC can be administered without regard to food or antacid use. (2.1)
- No dose adjustment is necessary when administering ULORIC to patients with mild to moderate renal or hepatic impairment. (2.2)

3 DOSAGE FORMS AND STRENGTHS

Tablet: 40 mg, 80 mg. (3)

4 CONTRAINDICATIONS

ULORIC is contraindicated in patients being treated with azathioprine, mercaptopurine, or theophylline. (4)

5 WARNINGS AND PRECAUTIONS

- Gout Flare: An increase in gout flares is frequently observed during initiation of anti-hyperuricemic agents, including ULORIC. If a gout flare occurs during treatment, ULORIC need not be discontinued. Prophylactic therapy (i.e., non-steroidal anti-inflammatory drug (NSAID) or colchicine upon initiation of treatment) may be beneficial for up to six months. (2.4, 5.1)
- Cardiovascular Events: A higher rate of cardiovascular thromboembolic events was observed in patients treated with ULORIC than allopurinol in clinical trials. Monitor for signs and symptoms of MI and stroke. (5.2)
- Liver Enzyme Elevation: Transaminase elevations have been observed in ULORIC-treated patients. Monitor liver function tests periodically. (5.3)

6 ADVERSE REACTIONS

Adverse reactions occurring in at least 1% of ULORIC-treated patients, and, at least 0.5% greater than placebo, are liver function abnormalities, nausea, arthralgia, and rash. (6.1)

To report SUSPECTED ADVERSE REACTIONS, contact Takeda Pharmaceuticals at 1-877-825-3327 or FDA at 1-800-FDA-1088 or www.fda.gov/medwatch

7 DRUG INTERACTIONS

Concomitant administration of ULORIC with XO substrate drugs, azathioprine, mercaptopurine, or theophylline could increase plasma concentrations of these drugs resulting in severe toxicity. (7)

8 USE IN SPECIFIC POPULATIONS

- There is insufficient data in patients with severe renal impairment. No studies have been conducted in patients with severe hepatic impairment. Caution should be exercised in these patients. (8.6, 8.7)
- No studies have been conducted in patients with secondary hyperuricemia (including patients being treated for Lesch-Nyhan syndrome or malignant disease, or in organ transplant recipients); therefore, ULORIC is not recommended for use in these patients. (8.8)

FULL PRESCRIBING INFORMATION

1 INDICATIONS AND USAGE

ULORIC® is a xanthine oxidase (XO) inhibitor indicated for the chronic management of hyperuricemia in patients with gout.

ULORIC is not recommended for the treatment of asymptomatic hyperuricemia.

2 DOSAGE AND ADMINISTRATION

2.1 Recommended Dose

For treatment of hyperuricemia in patients with gout, ULORIC is recommended at 40 mg or 80 mg once daily.

The recommended starting dose of ULORIC is 40 mg once daily. For patients who do not achieve a serum uric acid (sUA) less than 6 mg per dL after 2 weeks with 40 mg, ULORIC 80 mg is recommended.

ULORIC can be taken without regard to food or antacid use [see Clinical Pharmacology (12.3)].

2.2 Special Populations

No dose adjustment is necessary when administering ULORIC in patients with mild to moderate renal impairment [see Use in Specific Populations (8.6) and Clinical Pharmacology (12.3)]. The recommended starting dose of ULORIC is 40 mg once daily. For patients who do not achieve a sUA less than 6 mg per dL after 2 weeks with 40 mg, ULORIC 80 mg is recommended.

No dose adjustment is necessary in patients with mild to moderate hepatic impairment [see Use in Specific Populations (8.7) and Clinical Pharmacology (12.3)].

2.3 Uric Acid Level

Testing for the target serum uric acid level of less than 6 mg per dL may be performed as early as 2 weeks after initiating ULORIC therapy.

2.4 Gout Flares

Gout flares may occur after initiation of ULORIC due to changing serum uric acid levels resulting in mobilization of urate from tissue deposits. Flare prophylaxis with a non-steroidal anti-inflammatory drug (NSAID) or colchicine is recommended upon initiation of ULORIC. Prophylactic therapy may be beneficial for up to six months [see Clinical Studies (14.1)].

If a gout flare occurs during ULORIC treatment, ULORIC need not be discontinued. The gout flare should be managed concurrently, as appropriate for the individual patient [see Warnings and Precautions (5.1)].

3 DOSAGE FORMS AND STRENGTHS

- 40 mg tablets, light green to green, round shaped, debossed with "TAP" and "40"
- 80 mg tablets, light green to green, teardrop shaped, debossed with "TAP" and "80"

4 CONTRAINDICATIONS

ULORIC is contraindicated in patients being treated with azathioprine, mercaptopurine, or theophylline [see Drug Interactions (7)].

5 WARNINGS AND PRECAUTIONS

5.1 Gout Flare

After initiation of ULORIC, an increase in gout flares is frequently observed. This increase is due to reduction in serum uric acid levels resulting in mobilization of urate from tissue deposits.

In order to prevent gout flares when ULORIC is initiated, concurrent prophylactic treatment with an NSAID or colchicine is recommended [see Dosage and Administration (2.4)].

5.2 Cardiovascular Events

In the randomized controlled studies, there was a higher rate of cardiovascular thromboembolic events (cardiovascular deaths, non-fatal myocardial infarctions, and non-fatal strokes) in patients treated with ULORIC [0.74 per 100 P-Y (95% CI 0.36-1.37)] than allopurinol [0.60 per 100 P-Y (95% CI 0.16-1.53)] [see Adverse Reactions (6.1)]. A causal relationship with ULORIC has not been established. Monitor for signs and symptoms of myocardial infarction (MI) and stroke.

5.3 Liver Enzyme Elevations

During randomized controlled studies, transaminase elevations greater than 3 times the upper limit of normal (ULN) were observed (AST: 2%, 2%, and ALT: 3%, 2% in ULORIC and allopurinol-treated patients, respectively). No dose-effect relationship for these transaminase elevations was noted. Laboratory assessment of liver function is recommended at, for example, 2 and 4 months following initiation of ULORIC and periodically thereafter.

6 ADVERSE REACTIONS

6.1 Clinical Trials Experience

Because clinical trials are conducted under widely varying conditions, adverse reaction rates observed in the clinical trials of a drug cannot be directly compared to rates in the clinical trials of another drug and may not reflect the rates observed in practice.

A total of 2757 subjects with hyperuricemia and gout were treated with ULORIC 40 mg or 80 mg daily in clinical studies. For ULORIC 40 mg, 559 patients were treated for ≥ 6 months. For ULORIC 80 mg, 1377 subjects were treated for ≥ 6 months, 674 patients were treated for ≥ 1 year and 515 patients were treated for ≥ 2 years.

Most Common Adverse Reactions

In three randomized, controlled clinical studies (Studies 1, 2 and 3), which were 6 to 12 months in duration, the following adverse reactions were reported by the treating physician as related to study drug. Table 1 summarizes adverse reactions reported at a rate of at least 1% in ULORIC treatment groups and at least 0.5% greater than placebo.

Table 1: Adverse Reactions Occurring in ≥ 1% of ULORIC-Treated Patients and at Least 0.5% Greater than Seen in Patients Receiving Placebo in Controlled Studies
Adverse Reactions | Placebo | ULORIC |  | allopurinol [Of the subjects who received allopurinol, 10 received 100 mg, 145 received 200 mg, and 1122 received 300 mg, based on level of renal impairment.]
Adverse Reactions | (N=134) | 40 mg daily (N=757) | 80 mg daily (N=1279) | (N=1277)
Liver Function Abnormalities | 0.7% | 6.6% | 4.6% | 4.2%
Nausea | 0.7% | 1.1% | 1.3% | 0.8%
Arthralgia | 0% | 1.1% | 0.7% | 0.7%
Rash | 0.7% | 0.5% | 1.6% | 1.6%

The most common adverse reaction leading to discontinuation from therapy was liver function abnormalities in 1.8% of ULORIC 40 mg, 1.2% of ULORIC 80 mg, and in 0.9% of allopurinol-treated subjects.

In addition to the adverse reactions presented in Table 1, dizziness was reported in more than 1% of ULORIC-treated subjects although not at a rate more than 0.5% greater than placebo.

Less Common Adverse Reactions

In phase 2 and 3 clinical studies the following adverse reactions occurred in less than 1% of subjects and in more than one subject treated with doses ranging from 40 mg to 240 mg of ULORIC. This list also includes adverse reactions (less than 1% of subjects) associated with organ systems from Warnings and Precautions.

Blood and Lymphatic System Disorders: anemia, idiopathic thrombocytopenic purpura, leukocytosis/leukopenia, neutropenia, pancytopenia, splenomegaly, thrombocytopenia.

Cardiac Disorders: angina pectoris, atrial fibrillation/flutter, cardiac murmur, ECG abnormal, palpitations, sinus bradycardia, tachycardia.

Ear and Labyrinth Disorders: deafness, tinnitus, vertigo.

Eye Disorders: vision blurred.

Gastrointestinal Disorders: abdominal distention, abdominal pain, constipation, dry mouth, dyspepsia, flatulence, frequent stools, gastritis, gastroesophageal reflux disease, gastrointestinal discomfort, gingival pain, haematemesis, hyperchlorhydria, hematochezia, mouth ulceration, pancreatitis, peptic ulcer, vomiting.

General Disorders and Administration Site Conditions: asthenia, chest pain/discomfort, edema, fatigue, feeling abnormal, gait disturbance, influenza-like symptoms, mass, pain, thirst.

Hepatobiliary Disorders: cholelithiasis/cholecystitis, hepatic steatosis, hepatitis, hepatomegaly.

Immune System Disorder: hypersensitivity.

Infections and Infestations: herpes zoster.

Procedural Complications: contusion.

Metabolism and Nutrition Disorders: anorexia, appetite decreased/increased, dehydration, diabetes mellitus, hypercholesterolemia, hyperglycemia, hyperlipidemia, hypertriglyceridemia, hypokalemia, weight decreased/increased.

Musculoskeletal and Connective Tissue Disorders: arthritis, joint stiffness, joint swelling, muscle spasms/twitching/tightness/weakness, musculoskeletal pain/stiffness, myalgia.

Nervous System Disorders: altered taste, balance disorder, cerebrovascular accident, Guillain-Barré syndrome, headache, hemiparesis, hypoesthesia, hyposmia, lacunar infarction, lethargy, mental impairment, migraine, paresthesia, somnolence, transient ischemic attack, tremor.

Psychiatric Disorders: agitation, anxiety, depression, insomnia, irritability, libido decreased, nervousness, panic attack, personality change.

Renal and Urinary Disorders: hematuria, nephrolithiasis, pollakiuria, proteinuria, renal failure, renal insufficiency, urgency, incontinence.

Reproductive System and Breast Changes: breast pain, erectile dysfunction, gynecomastia.

Respiratory, Thoracic and Mediastinal Disorders: bronchitis, cough, dyspnea, epistaxis, nasal dryness, paranasal sinus hypersecretion, pharyngeal edema, respiratory tract congestion, sneezing, throat irritation, upper respiratory tract infection.

Skin and Subcutaneous Tissue Disorders: alopecia, angio-edema, dermatitis, dermographism, ecchymosis, eczema, hair color changes, hair growth abnormal, hyperhidrosis, peeling skin, petechiae, photosensitivity, pruritus, purpura, skin discoloration/altered pigmentation, skin lesion, skin odor abnormal, urticaria.

Vascular Disorders: flushing, hot flush, hypertension, hypotension.

Laboratory Parameters: activated partial thromboplastin time prolonged, creatine increased, bicarbonate decreased, sodium increased, EEG abnormal, glucose increased, cholesterol increased, triglycerides increased, amylase increased, potassium increased, TSH increased, platelet count decreased, hematocrit decreased, hemoglobin decreased, MCV increased, RBC decreased, creatinine increased, blood urea increased, BUN/creatinine ratio increased, creatine phosphokinase (CPK) increased, alkaline phosphatase increased, LDH increased, PSA increased, urine output increased/decreased, lymphocyte count decreased, neutrophil count decreased, WBC increased/decreased, coagulation test abnormal, low density lipoprotein (LDL) increased, prothrombin time prolonged, urinary casts, urine positive for white blood cells and protein.

Cardiovascular Safety

Cardiovascular events and deaths were adjudicated to one of the pre-defined endpoints from the Anti-Platelet Trialists' Collaborations (APTC) (cardiovascular death, non-fatal myocardial infarction, and non-fatal stroke) in the randomized controlled and long-term extension studies. In the Phase 3 randomized controlled studies, the incidences of adjudicated APTC events per 100 patient-years of exposure were: Placebo 0 (95% CI 0.00-6.16), ULORIC 40 mg 0 (95% CI 0.00-1.08), ULORIC 80 mg 1.09 (95% CI 0.44-2.24), and allopurinol 0.60 (95% CI 0.16-1.53).

In the long-term extension studies, the incidences of adjudicated APTC events were: ULORIC 80 mg 0.97 (95% CI 0.57-1.56), and allopurinol 0.58 (95% CI 0.02-3.24).

Overall, a higher rate of APTC events was observed in ULORIC than in allopurinol-treated patients. A causal relationship with ULORIC has not been established. Monitor for signs and symptoms of MI and stroke.

7 DRUG INTERACTIONS

7.1 Xanthine Oxidase Substrate Drugs

ULORIC is an XO inhibitor. Drug interaction studies of ULORIC with drugs that are metabolized by XO (e.g., theophylline, mercaptopurine, azathioprine) have not been conducted. Inhibition of XO by ULORIC may cause increased plasma concentrations of these drugs leading to toxicity [see Clinical Pharmacology (12.3)]. ULORIC is contraindicated in patients being treated with azathioprine, mercaptopurine, or theophylline [see Contraindications (4)].

7.2 Cytotoxic Chemotherapy Drugs

Drug interaction studies of ULORIC with cytotoxic chemotherapy have not been conducted. No data are available regarding the safety of ULORIC during cytotoxic chemotherapy.

7.3 In Vivo Drug Interaction Studies

Based on drug interaction studies in healthy subjects, ULORIC does not have clinically significant interactions with colchicine, naproxen, indomethacin, hydrochlorothiazide, warfarin or desipramine [see Clinical Pharmacology (12.3)]. Therefore, ULORIC may be used concomitantly with these medications.

8 USE IN SPECIFIC POPULATIONS

8.1 Pregnancy

TERATOGENIC EFFECTS

Pregnancy Category C: There are no adequate and well-controlled studies in pregnant women. ULORIC should be used during pregnancy only if the potential benefit justifies the potential risk to the fetus.

Febuxostat was not teratogenic in rats and rabbits at oral doses up to 48 mg per kg (40 and 51 times the human plasma exposure at 80 mg per day for equal body surface area, respectively) during organogenesis. However, increased neonatal mortality and a reduction in the neonatal body weight gain were observed when pregnant rats were treated with oral doses up to 48 mg per kg (40 times the human plasma exposure at 80 mg per day) during organogenesis and through lactation period.

8.3 Nursing Mothers

Febuxostat is excreted in the milk of rats. It is not known whether this drug is excreted in human milk. Because many drugs are excreted in human milk, caution should be exercised when ULORIC is administered to a nursing woman.

8.4 Pediatric Use

Safety and effectiveness in pediatric patients under 18 years of age have not been established.

8.5 Geriatric Use

No dose adjustment is necessary in elderly patients. Of the total number of subjects in clinical studies of ULORIC, 16 percent were 65 and over, while 4 percent were 75 and over. Comparing subjects in different age groups, no clinically significant differences in safety or effectiveness were observed but greater sensitivity of some older individuals cannot be ruled out. The Cmax and AUC24 of febuxostat following multiple oral doses of ULORIC in geriatric subjects (≥ 65 years) were similar to those in younger subjects (18-40 years) [see Clinical Pharmacology (12.3)].

8.6 Renal Impairment

No dose adjustment is necessary in patients with mild or moderate renal impairment (Clcr 30-89 mL per min). The recommended starting dose of ULORIC is 40 mg once daily. For patients who do not achieve a sUA less than 6 mg per dL after 2 weeks with 40 mg, ULORIC 80 mg is recommended.

There are insufficient data in patients with severe renal impairment (Clcr less than 30 mL per min); therefore, caution should be exercised in these patients [see Clinical Pharmacology (12.3)].

8.7 Hepatic Impairment

No dose adjustment is necessary in patients with mild or moderate hepatic impairment (Child-Pugh Class A or B). No studies have been conducted in patients with severe hepatic impairment (Child-Pugh Class C); therefore, caution should be exercised in these patients [see Clinical Pharmacology (12.3)].

8.8 Secondary Hyperuricemia

No studies have been conducted in patients with secondary hyperuricemia (including organ transplant recipients); ULORIC is not recommended for use in patients whom the rate of urate formation is greatly increased (e.g., malignant disease and its treatment, Lesch-Nyhan syndrome). The concentration of xanthine in urine could, in rare cases, rise sufficiently to allow deposition in the urinary tract.

10 OVERDOSAGE

ULORIC was studied in healthy subjects in doses up to 300 mg daily for seven days without evidence of dose-limiting toxicities. No overdose of ULORIC was reported in clinical studies. Patients should be managed by symptomatic and supportive care should there be an overdose.

11 DESCRIPTION

ULORIC (febuxostat) is a xanthine oxidase inhibitor. The active ingredient in ULORIC is 2-[3-cyano-4-(2-methylpropoxy) phenyl]-4-methylthiazole-5-carboxylic acid, with a molecular weight of 316.38. The empirical formula is C16H16N2O3S.

The chemical structure is:

Febuxostat is a non-hygroscopic, white crystalline powder that is freely soluble in dimethylformamide; soluble in dimethylsulfoxide; sparingly soluble in ethanol; slightly soluble in methanol and acetonitrile; and practically insoluble in water. The melting range is 205°C to 208°C.

ULORIC tablets for oral use contain the active ingredient, febuxostat, and are available in two dosage strengths, 40 mg and 80 mg. Inactive ingredients include lactose monohydrate, microcrystalline cellulose, hydroxypropyl cellulose, sodium croscarmellose, silicon dioxide and magnesium stearate. ULORIC tablets are coated with Opadry II, green.

12 CLINICAL PHARMACOLOGY

12.1 Mechanism of Action

ULORIC, a xanthine oxidase inhibitor, achieves its therapeutic effect by decreasing serum uric acid. ULORIC is not expected to inhibit other enzymes involved in purine and pyrimidine synthesis and metabolism at therapeutic concentrations.

12.2 Pharmacodynamics

Effect on Uric Acid and Xanthine Concentrations: In healthy subjects, ULORIC resulted in a dose dependent decrease in 24-hour mean serum uric acid concentrations, and an increase in 24-hour mean serum xanthine concentrations. In addition, there was a decrease in the total daily urinary uric acid excretion. Also, there was an increase in total daily urinary xanthine excretion. Percent reduction in 24-hour mean serum uric acid concentrations was between 40% to 55% at the exposure levels of 40 mg and 80 mg daily doses.

Effect on Cardiac Repolarization: The effect of ULORIC on cardiac repolarization as assessed by the QTc interval was evaluated in normal healthy subjects and in patients with gout. ULORIC in doses up to 300 mg daily, at steady state, did not demonstrate an effect on the QTc interval.

12.3 Pharmacokinetics

In healthy subjects, maximum plasma concentrations (Cmax) and AUC of febuxostat increased in a dose proportional manner following single and multiple doses of 10 mg to 120 mg. There is no accumulation when therapeutic doses are administered every 24 hours. Febuxostat has an apparent mean terminal elimination half-life (t1/2) of approximately 5 to 8 hours. Febuxostat pharmacokinetic parameters for patients with hyperuricemia and gout estimated by population pharmacokinetic analyses were similar to those estimated in healthy subjects.

Absorption: The absorption of radiolabeled febuxostat following oral dose administration was estimated to be at least 49% (based on total radioactivity recovered in urine). Maximum plasma concentrations of febuxostat occurred between 1 to 1.5 hours post-dose. After multiple oral 40 mg and 80 mg once daily doses, Cmax is approximately 1.6 ± 0.6 mcg per mL (N=30), and 2.6 ± 1.7 mcg per mL (N=227), respectively. Absolute bioavailability of the febuxostat tablet has not been studied.

Following multiple 80 mg once daily doses with a high fat meal, there was a 49% decrease in Cmax and an 18% decrease in AUC, respectively. However, no clinically significant change in the percent decrease in serum uric acid concentration was observed (58% fed vs. 51% fasting). Thus, ULORIC may be taken without regard to food.

Concomitant ingestion of an antacid containing magnesium hydroxide and aluminum hydroxide with an 80 mg single dose of ULORIC has been shown to delay absorption of febuxostat (approximately 1 hour) and to cause a 31% decrease in Cmax and a 15% decrease in AUC∞. As AUC rather than Cmax was related to drug effect, change observed in AUC was not considered clinically significant. Therefore, ULORIC may be taken without regard to antacid use.

Distribution: The mean apparent steady state volume of distribution (Vss/F) of febuxostat was approximately 50 L (CV ~40%). The plasma protein binding of febuxostat is approximately 99.2%, (primarily to albumin), and is constant over the concentration range achieved with 40 mg and 80 mg doses.

Metabolism: Febuxostat is extensively metabolized by both conjugation via uridine diphosphate glucuronosyltransferase (UGT) enzymes including UGT1A1, UGT1A3, UGT1A9, and UGT2B7 and oxidation via cytochrome P450 (CYP) enzymes including CYP1A2, 2C8 and 2C9 and non-P450 enzymes. The relative contribution of each enzyme isoform in the metabolism of febuxostat is not clear. The oxidation of the isobutyl side chain leads to the formation of four pharmacologically active hydroxy metabolites, all of which occur in plasma of humans at a much lower extent than febuxostat.

In urine and feces, acyl glucuronide metabolites of febuxostat (~35% of the dose), and oxidative metabolites, 67M-1 (~10% of the dose), 67M-2 (~11% of the dose), and 67M-4, a secondary metabolite from 67M-1, (~14% of the dose) appeared to be the major metabolites of febuxostat in vivo.

Elimination: Febuxostat is eliminated by both hepatic and renal pathways. Following an 80 mg oral dose of ^14C-labeled febuxostat, approximately 49% of the dose was recovered in the urine as unchanged febuxostat (3%), the acyl glucuronide of the drug (30%), its known oxidative metabolites and their conjugates (13%), and other unknown metabolites (3%). In addition to the urinary excretion, approximately 45% of the dose was recovered in the feces as the unchanged febuxostat (12%), the acyl glucuronide of the drug (1%), its known oxidative metabolites and their conjugates (25%), and other unknown metabolites (7%).

The apparent mean terminal elimination half-life (t1/2) of febuxostat was approximately 5 to 8 hours.

Special Populations

Pediatric Use: The pharmacokinetics of ULORIC in patients under the age of 18 years have not been studied.

Geriatric Use: The Cmax and AUC of febuxostat and its metabolites following multiple oral doses of ULORIC in geriatric subjects (≥ 65 years) were similar to those in younger subjects (18-40 years). In addition, the percent decrease in serum uric acid concentration was similar between elderly and younger subjects. No dose adjustment is necessary in geriatric patients [see Use in Specific Populations (8.5)].

Renal Impairment: Following multiple 80 mg doses of ULORIC in healthy subjects with mild (Clcr 50-80 mL per min), moderate (Clcr 30-49 mL per min) or severe renal impairment (Clcr 10-29 mL per min), the Cmax of febuxostat did not change relative to subjects with normal renal function (Clcr greater than 80 mL per min). AUC and half-life of febuxostat increased in subjects with renal impairment in comparison to subjects with normal renal function, but values were similar among three renal impairment groups. Mean febuxostat AUC values were up to 1.8 times higher in subjects with renal impairment compared to those with normal renal function. Mean Cmax and AUC values for 3 active metabolites increased up to 2- and 4-fold, respectively. However, the percent decrease in serum uric acid concentration for subjects with renal impairment was comparable to those with normal renal function (58% in normal renal function group and 55% in the severe renal function group).

No dose adjustment is necessary in patients with mild to moderate renal impairment [see Dosage and Administration (2) and Use in Specific Populations (8.6)]. The recommended starting dose of ULORIC is 40 mg once daily. For patients who do not achieve a sUA less than 6 mg per dL after 2 weeks with 40 mg, ULORIC 80 mg is recommended. There is insufficient data in patients with severe renal impairment; caution should be exercised in those patients [see Use in Specific Populations (8.6)].

ULORIC has not been studied in end stage renal impairment patients who are on dialysis.

Hepatic Impairment: Following multiple 80 mg doses of ULORIC in patients with mild (Child-Pugh Class A) or moderate (Child-Pugh Class B) hepatic impairment, an average of 20-30% increase was observed for both Cmax and AUC24 (total and unbound) in hepatic impairment groups compared to subjects with normal hepatic function. In addition, the percent decrease in serum uric acid concentration was comparable between different hepatic groups (62% in healthy group, 49% in mild hepatic impairment group, and 48% in moderate hepatic impairment group). No dose adjustment is necessary in patients with mild or moderate hepatic impairment. No studies have been conducted in subjects with severe hepatic impairment (Child-Pugh Class C); caution should be exercised in those patients [see Use in Specific Populations (8.7)].

Gender: Following multiple oral doses of ULORIC, the Cmax and AUC24 of febuxostat were 30% and 14% higher in females than in males, respectively. However, weight-corrected Cmax and AUC were similar between the genders. In addition, the percent decrease in serum uric acid concentrations was similar between genders. No dose adjustment is necessary based on gender.

Race: No specific pharmacokinetic study was conducted to investigate the effects of race.

Drug-Drug Interactions

Effect of ULORIC on Other Drugs

Xanthine Oxidase Substrate Drugs-Azathioprine, Mercaptopurine, and Theophylline: Febuxostat is an XO inhibitor. Drug interaction studies of ULORIC with drugs that are metabolized by XO (e.g., theophylline, mercaptopurine, azathioprine) have not been conducted. Inhibition of XO by ULORIC may cause increased plasma concentrations of these drugs leading to toxicity. ULORIC is contraindicated in patients being treated with azathioprine, mercaptopurine, and theophylline [see Contraindications (4) and Drug Interactions (7)].

Azathioprine and mercaptopurine undergo metabolism via three major metabolic pathways, one of which is mediated by XO. Although ULORIC drug interaction studies with azathioprine and mercaptopurine have not been conducted, concomitant administration of allopurinol [a xanthine oxidase inhibitor] with azathioprine or mercaptopurine has been reported to substantially increase plasma concentrations of these drugs. Because ULORIC is a xanthine oxidase inhibitor, it could inhibit the XO-mediated metabolism of azathioprine and mercaptopurine leading to increased plasma concentrations of azathioprine or mercaptopurine that could result in severe toxicity.

Theophylline is a CYP1A2 and XO substrate. Although no ULORIC drug interaction study with theophylline has been conducted, concomitant administration of theophylline with allopurinol, a xanthine oxidase inhibitor at doses ≥ 600 mg per day, has been reported to increase theophylline plasma concentrations. Because ULORIC is a xanthine oxidase inhibitor and theophylline is a low therapeutic index drug, ULORIC could inhibit the XO-mediated metabolism of theophylline leading to increased plasma concentrations of theophylline that could induce severe theophylline toxicity.

P450 Substrate Drugs: In vitro studies have shown that febuxostat does not inhibit P450 enzymes CYP1A2, 2C9, 2C19, 2D6, or 3A4 and it also does not induce CYP1A2, 2B6, 2C9, 2C19, or 3A4 at clinically relevant concentrations. As such, pharmacokinetic interactions between ULORIC and drugs metabolized by these CYP enzymes are unlikely.

Effect of Other Drugs on ULORIC

Febuxostat is metabolized by conjugation and oxidation via multiple metabolizing enzymes. The relative contribution of each enzyme isoform is not clear. Drug interactions between ULORIC and a drug that inhibits or induces one particular enzyme isoform is in general not expected.

In Vivo Drug Interaction Studies

Colchicine: No dose adjustment is necessary for either ULORIC or colchicine when the two drugs are co-administered. Administration of ULORIC (40 mg once daily) with colchicine (0.6 mg twice daily) resulted in an increase of 12% in Cmax and 7% in AUC24 of febuxostat. In addition, administration of colchicine (0.6 mg twice daily) with ULORIC (120 mg daily) resulted in less than 11% change in Cmax or AUC of colchicine for both AM and PM doses. These changes were not considered clinically significant.

Naproxen: No dose adjustment is necessary for ULORIC or naproxen when the two drugs are co-administered. Administration of ULORIC (80 mg once daily) with naproxen (500 mg twice daily) resulted in a 28% increase in Cmax and a 40% increase in AUC of febuxostat. The increases were not considered clinically significant. In addition, there were no significant changes in the Cmax or AUC of naproxen (less than 2%).

Indomethacin: No dose adjustment is necessary for either ULORIC or indomethacin when these two drugs are co-administered. Administration of ULORIC (80 mg once daily) with indomethacin (50 mg twice daily) did not result in any significant changes in Cmax or AUC of febuxostat or indomethacin (less than 7%).

Hydrochlorothiazide: No dose adjustment is necessary for ULORIC when co-administered with hydrochlorothiazide. Administration of ULORIC (80 mg) with hydrochlorothiazide (50 mg) did not result in any clinically significant changes in Cmax or AUC of febuxostat (less than 4%), and serum uric acid concentrations were not substantially affected.

Warfarin: No dose adjustment is necessary for warfarin when co-administered with ULORIC. Administration of ULORIC (80 mg once daily) with warfarin had no effect on the pharmacokinetics of warfarin in healthy subjects. INR and Factor VII activity were also not affected by the co-administration of ULORIC.

Desipramine: Co-administration of drugs that are CYP2D6 substrates (such as desipramine) with ULORIC are not expected to require dose adjustment. Febuxostat was shown to be a weak inhibitor of CYP2D6 in vitro and in vivo. Administration of ULORIC (120 mg once daily) with desipramine (25 mg) resulted in an increase in Cmax (16%) and AUC (22%) of desipramine, which was associated with a 17% decrease in the 2-hydroxydesipramine to desipramine metabolic ratio (based on AUC).

13 NONCLINICAL TOXICOLOGY

13.1 Carcinogenesis, Mutagenesis, Impairment of Fertility

Carcinogenesis: Two-year carcinogenicity studies were conducted in F344 rats and B6C3F1 mice. Increased transitional cell papilloma and carcinoma of urinary bladder was observed at 24 mg per kg (25 times the human plasma exposure at maximum recommended human dose of 80 mg per day) and 18.75 mg per kg (12.5 times the human plasma exposure at 80 mg per day) in male rats and female mice, respectively. The urinary bladder neoplasms were secondary to calculus formation in the kidney and urinary bladder.

Mutagenesis: Febuxostat showed a positive mutagenic response in a chromosomal aberration assay in a Chinese hamster lung fibroblast cell line with and without metabolic activation in vitro. Febuxostat was negative in the in vitro Ames assay and chromosomal aberration test in human peripheral lymphocytes, and L5178Y mouse lymphoma cell line, and in vivo tests in mouse micronucleus, rat unscheduled DNA synthesis and rat bone marrow cells.

Impairment of Fertility: Febuxostat at oral doses up to 48 mg per kg per day (approximately 35 times the human plasma exposure at 80 mg per day) had no effect on fertility and reproductive performance of male and female rats.

13.2 Animal Toxicology and/or Pharmacology

A 12-month toxicity study in beagle dogs showed deposition of xanthine crystals and calculi in kidneys at 15 mg per kg (approximately 4 times the human plasma exposure at 80 mg per day). A similar effect of calculus formation was noted in rats in a six-month study due to deposition of xanthine crystals at 48 mg per kg (approximately 35 times the human plasma exposure at 80 mg per day).

14 CLINICAL STUDIES

A serum uric acid level of less than 6 mg per dL is the goal of anti-hyperuricemic therapy and has been established as appropriate for the treatment of gout.

14.1 Management of Hyperuricemia in Gout

The efficacy of ULORIC was demonstrated in three randomized, double-blind, controlled trials in patients with hyperuricemia and gout. Hyperuricemia was defined as a baseline serum uric acid level ≥ 8 mg per dL.

Study 1 randomized patients to: ULORIC 40 mg daily, ULORIC 80 mg daily, or allopurinol (300 mg daily for patients with estimated creatinine clearance (Clcr) ≥ 60 mL per min or 200 mg daily for patients with estimated Clcr ≥ 30 mL per min and ≤ 59 mL per min). The duration of Study 1 was 6 months.

Study 2 randomized patients to: placebo, ULORIC 80 mg daily, ULORIC 120 mg daily, ULORIC 240 mg daily or allopurinol (300 mg daily for patients with a baseline serum creatinine ≤ 1.5 mg per dL or 100 mg daily for patients with a baseline serum creatinine greater than 1.5 mg per dL and ≤ 2 mg per dL). The duration of Study 2 was 6 months.

Study 3, a 1-year study, randomized patients to: ULORIC 80 mg daily, ULORIC 120 mg daily, or allopurinol 300 mg daily. Subjects who completed Study 2 and Study 3 were eligible to enroll in a phase 3 long-term extension study in which subjects received treatment with ULORIC for over three years.

In all three studies, subjects received naproxen 250 mg twice daily or colchicine 0.6 mg once or twice daily for gout flare prophylaxis. In Study 1 the duration of prophylaxis was 6 months; in Study 2 and Study 3 the duration of prophylaxis was 8 weeks.

The efficacy of ULORIC was also evaluated in a 4 week dose ranging study which randomized patients to: placebo, ULORIC 40 mg daily, ULORIC 80 mg daily, or ULORIC 120 mg daily. Subjects who completed this study were eligible to enroll in a long-term extension study in which subjects received treatment with ULORIC for up to five years.

Patients in these studies were representative of the patient population for which ULORIC use is intended. Table 2 summarizes the demographics and baseline characteristics for the subjects enrolled in the studies.

Table 2: Patient Demographics and Baseline Characteristics in Study 1, Study 2 and Study 3
Male |  | 95%
Race: | Caucasian | 80%
 | African American | 10%
Ethnicity: | Hispanic or Latino | 7%
Alcohol User |  | 67%
Mild to Moderate Renal Insufficiency [percent with estimated Clcr less than 90 mL per min] |  | 59%
History of Hypertension |  | 49%
History of Hyperlipidemia |  | 38%
BMI ≥ 30 kg per m^2 |  | 63%
Mean BMI |  | 33 kg per m^2
Baseline sUA ≥ 10 mg per dL |  | 36%
Mean baseline sUA |  | 9.7 mg per dL
Experienced a gout flare in previous year |  | 85%

Serum Uric Acid Level less than 6 mg per dL at Final Visit: ULORIC 80 mg was superior to allopurinol in lowering serum uric acid to less than 6 mg per dL at the final visit. ULORIC 40 mg daily, although not superior to allopurinol, was effective in lowering serum uric acid to less than 6 mg per dL at the final visit (Table 3).

Table 3: Proportion of Patients with Serum Uric Acid Levels Less Than 6 mg per dL at Final Visit
 |  |  |  |  | Difference in Proportion (95% CI)
Study [Randomization was balanced between treatment groups, except in Study 2 in which twice as many patients were randomized to each of the active treatment groups compared to placebo.] | ULORIC 40 mg daily | ULORIC 80 mg daily | allopurinol | Placebo | ULORIC 40 mg vs allopurinol | ULORIC 80 mg vs allopurinol
Study 1 (6 months) (N=2268) | 45% | 67% | 42% |  | 3% (-2%, 8%) | 25% (20%, 30%)
Study 2 (6 months) (N=643) |  | 72% | 39% | 1% |  | 33% (26%, 42%)
Study 3 (12 months) (N=491) |  | 74% | 36% |  |  | 38% (30%, 46%)

In 76% of ULORIC 80 mg patients, reduction in serum uric acid levels to less than 6 mg per dL was noted by the Week 2 visit. Average serum uric acid levels were maintained at 6 mg per dL or below throughout treatment in 83% of these patients.

In all treatment groups, fewer subjects with higher baseline serum urate levels (≥ 10 mg per dL) and/or tophi achieved the goal of lowering serum uric acid to less than 6 mg per dL at the final visit; however, a higher proportion achieved a serum uric acid less than 6 mg per dL with ULORIC 80 mg than with ULORIC 40 mg or allopurinol.

Study 1 evaluated efficacy in patients with mild to moderate renal impairment (i.e., baseline estimated Clcr less than 90 mL per minute). The results in this sub-group of patients are shown in Table 4.

Table 4: Proportion of Patients with Serum Uric Acid Levels Less Than 6 mg per dL in Patients with Mild or Moderate Renal Impairment at Final Visit
 |  |  | Difference in Proportion (95% CI)
ULORIC 40 mg daily (N=479) | ULORIC 80 mg daily (N=503) | allopurinol [Allopurinol patients (n=145) with estimated Clcr ≥ 30 mL per min and Clcr ≤ 59 mL per min were dosed at 200 mg daily.] 300 mg daily (N=501) | ULORIC 40 mg vs allopurinol | ULORIC 80 mg vs allopurinol
50% | 72% | 42% | 7% (1%, 14%) | 29% (23%, 35%)

16 HOW SUPPLIED/STORAGE AND HANDLING

ULORIC 80 mg tablets are light green to green in color, teardrop shaped, debossed with "TAP" on one side and "80" on the other side and supplied as:

NDC Number | Size
21695-516-30 | Bottle of 30 Tablets

STORAGE AND HANDLING

Protect from light. Store at 25°C (77°F); excursions permitted to 15°– 30°C (59°– 86°F) [See USP Controlled Room Temperature]

17 PATIENT COUNSELING INFORMATION

[see FDA-Approved Patient Labeling (17.2)]

17.1 General Information

Patients should be advised of the potential benefits and risks of ULORIC. Patients should be informed about the potential for gout flares, elevated liver enzymes and adverse cardiovascular events after initiation of ULORIC therapy.

Concomitant prophylaxis with an NSAID or colchicine for gout flares should be considered.

Patients should be instructed to inform their healthcare professional if they develop a rash, chest pain, shortness of breath or neurologic symptoms suggesting a stroke. Patients should be instructed to inform their healthcare professional of any other medications they are currently taking with ULORIC, including over-the-counter medications.

Patient Information
ULORIC® (Ū – 'lor – ik)
(febuxostat) tablets

Read the Patient Information that comes with ULORIC before you start taking it and each time you get a refill. There may be new information. This information does not take the place of talking with your healthcare provider about your medical condition or your treatment.

What is ULORIC?

ULORIC is a prescription medicine called a xanthine oxidase (XO) inhibitor, used to lower blood uric acid levels in adults with gout.

It is not known if ULORIC is safe and effective in children under 18 years of age.

Who should not take ULORIC?

Do not take ULORIC if you:

- take Azathioprine (Azasan®, Imuran®)
- take Mercaptopurine (Purinethol®)
- take Theophylline (Theo-24®, Elixophyllin®, Theochron®, Theolair®, Uniphyl®)

It is not known if ULORIC is safe and effective in children under 18 years of age.

What should I tell my healthcare provider before taking ULORIC?

Before taking ULORIC tell your healthcare provider about all of your medical conditions, including if you:

- have liver or kidney problems
- have a history of heart disease or stroke
- are pregnant or plan to become pregnant. It is not known if ULORIC will harm your unborn baby. Talk with your healthcare provider if you are pregnant or plan to become pregnant.
- are breast-feeding or plan to breast-feed. It is not known if ULORIC passes into your breast milk. You and your healthcare provider should decide if you should take ULORIC while breast-feeding.

Tell your healthcare provider about all the medicines you take, including prescription and non-prescription medicines, vitamins, and herbal supplements. ULORIC may affect the way other medicines work, and other medicines may affect how ULORIC works.

Know the medicines you take. Keep a list of them and show it to your healthcare provider and pharmacist when you get a new medicine.

How should I take ULORIC?

- Take ULORIC exactly as your healthcare provider tells you to take it.
- ULORIC can be taken with or without food.
- ULORIC can be taken with antacids.
- Your gout may flare up when you start taking ULORIC, do not stop taking your ULORIC even if you have a flare. Your healthcare provider may give you other medicines to help prevent your gout flares.
- Your healthcare provider may do certain tests while you take ULORIC.

What are the possible side effects of ULORIC?

Heart problems. A small number of heart attacks, strokes and heart-related deaths were seen in clinical studies. It is not certain that ULORIC caused these events.

The most common side effects of ULORIC include:

- liver problems
- nausea
- gout flares
- joint pain
- rash

Tell your healthcare provider if you have any side effect that bothers you or that does not go away. These are not all of the possible side effects of ULORIC. For more information, ask your healthcare provider or pharmacist.

Call your doctor for medical advice about side effects. You may report side effects to the FDA at 1-800-FDA-1088.

How should I store ULORIC?

Store ULORIC between 59°F - 86°F (15°C - 30°C).

Keep ULORIC out of the light.

Keep ULORIC and all medicines out of the reach of children.

General information about the safe and effective use of ULORIC

Medicines are sometimes prescribed for purposes other than those listed in a patient information leaflet. Do not use ULORIC for a condition for which it was not prescribed. Do not give ULORIC to other people, even if they have the same symptoms that you have. It may harm them.

This patient information leaflet summarizes the most important information about ULORIC. If you would like more information about ULORIC talk with your healthcare provider. You can ask your healthcare provider or pharmacist for information about ULORIC that is written for health professionals. For more information go to www.uloric.com, or call 1-877-825-3327.

What are the ingredients in ULORIC?

Active Ingredient: febuxostat

Inactive ingredients include: lactose monohydrate, microcrystalline cellulose, hydroxypropyl cellulose, sodium croscarmellose, silicon dioxide, magnesium stearate, and Opadry II, green

Distributed by
Takeda Pharmaceuticals America, Inc.
Deerfield, IL 60015

U.S. Patent Nos. - 6,225,474; 7,361,676; 5,614,520.

ULORIC® is a registered trademark of Teijin Pharma Limited and used under license by Takeda Pharmaceuticals America, Inc.

All other trademark names are the property of their respective owners

©2009 Takeda Pharmaceuticals America, Inc.

PI1114 R1
February 2009

Repackaged by Rebel Distributors Corp

Thousand Oaks, CA 91320

PACKAGE LABEL

PRINCIPAL DISPLAY PANEL - 80 mg 30 Tablet Bottle

30 Tablets
Rx only

Uloric®
febuxostat
tablets

80 mg